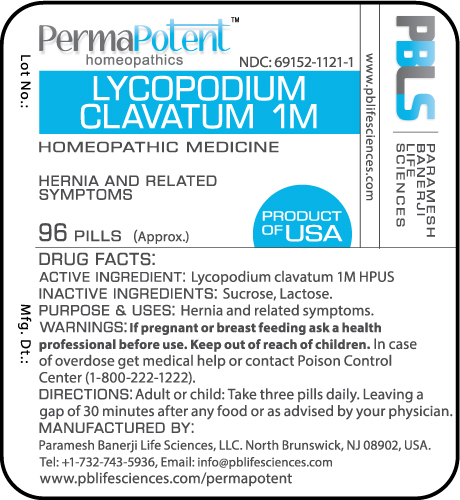 DRUG LABEL: Lycopodium clavatum 1M
NDC: 69152-1121 | Form: PELLET
Manufacturer: Paramesh Banerji Life Sciences LLC
Category: homeopathic | Type: HUMAN OTC DRUG LABEL
Date: 20160331

ACTIVE INGREDIENTS: LYCOPODIUM CLAVATUM SPORE 1 [hp_M]/1 1
INACTIVE INGREDIENTS: LACTOSE; SUCROSE

DRUG FACTS: Active Ingredient

Lycopodium clavatum 1M HPUS

Inactive Ingredients

Sucrose, Lactose

Purpose

Hernia and related symptoms

Uses

Hernia and related symptoms

Warnings

If pregnant or breast feeding ask a health professional before use.

Keep out of reach of children. In case of overdose, get medical help or contact a Poison Control Center (1-800-222-1222) right away.

Direction

Adult or child: Take three pills daily. Leaving a gap of 30 minutes after any food or as advised by your physician.

Manufactured by

Paramesh Banerji Life Sciences, LLC.

North Brunswick, NJ 08902, USA.

Tel: +1-732-743-5936,

Email: info@pblifesciences.com

www.pblifesciences.com/permapotent

Principal Display Panel

NDC: 69152-1121-1

Lycopodium clavatum 1M

Homeopathic Medicine

Hernia and related symptoms

96 Pills (Approx.)

Product of USA